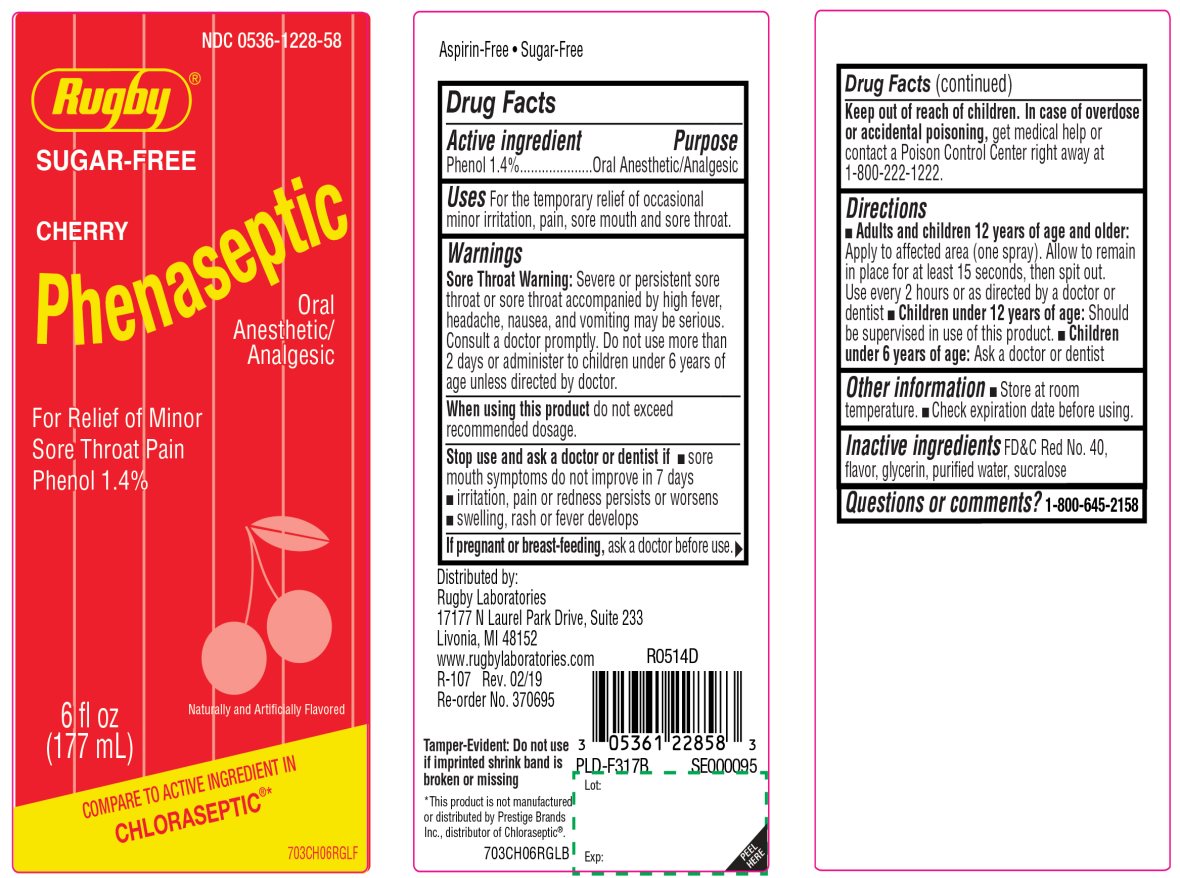 DRUG LABEL: Rugby

NDC: 0536-1228 | Form: SPRAY
Manufacturer: RUGBY LABORATORIES
Category: otc | Type: HUMAN OTC DRUG LABEL
Date: 20251025

ACTIVE INGREDIENTS: PHENOL 1.4 g/100 mL
INACTIVE INGREDIENTS: FD&C RED NO. 40; GLYCERIN; WATER; SUCRALOSE

Rugby SUGAR-FREE CHERRY PHENASEPTIC

Active ingredient

Phenol 1.4%

Purpose

Oral Anesthetic/Analgesic

Uses

For the temporarily relief of occasional minor irritation, pain, sore mouth and sore throat.

Warnings

Sore throat warning:Severe or persistent sore throat or sore throat accompanied by high fever, headache, nausea, and vomiting may be serious. Consult a doctor promptly. Do not use more than 2 days or administer to children under 6 years of age unless directed by a doctor.

When using this product,

do not exceed recommended dosage.

Stop use and ask a dentist or doctor if

- sore mouth symptoms do not improve in 7 days
- irritation, pain or redness persists or worsens
- swelling, rash or fever develops

If pregnant or breast-feeding,

ask a doctor before use.

Keep out of reach of children.

In case of overdose or accidental poisoning,get medical help or contact a Poison Control Center (1-800-222-1222) right away.

Directions

- Adults and children 12 years of age and older
  - apply to affected area (one spray)
  - allow to remain in place for at least 15 seconds, then spit out
  - use every 2 hours as directed by a doctor or dentist
- Children under 12 years of age: should be supervised in the use of this product
- Children under 6 years of age, Ask a doctor or dentist

Other information

- Store at room temperature.
- Check expiration date before using.

Inactive ingredients

FD&C Red No. 40, flavor, glycerin, purified water, sucralose.

Questions or comments?

1-800-645-2158

Principal Display Panel

*COMPARE TO THE ACTIVE INGREDIENT IN CHLORASEPTIC®

NDC# 0536-1228-58

Rugby®

SUGAR-FREE

CHERRY Phenaseptic

Oral Anesthetic/Analgesic

For Relief of Minor

Sore Throat Pain

Phenol 1.4%

Naturally and Artificially Flavored

Aspirin Free

Sugar Free

6 FL OZ (177 mL)

*This product is not manufactured or distributed by Prestige Brands, Inc., distributor of Chloraseptic®.

TAMPER EVIDENT: DO NOT USE IF IMPRINTED SHRINK BAND IS BROKEN OR MISSING

Distributed by:

Rugby Laboratories

17177 N Laurel Park Drive, Suite 233

Livonia, MI 48152

www.rugbylaboratories.com